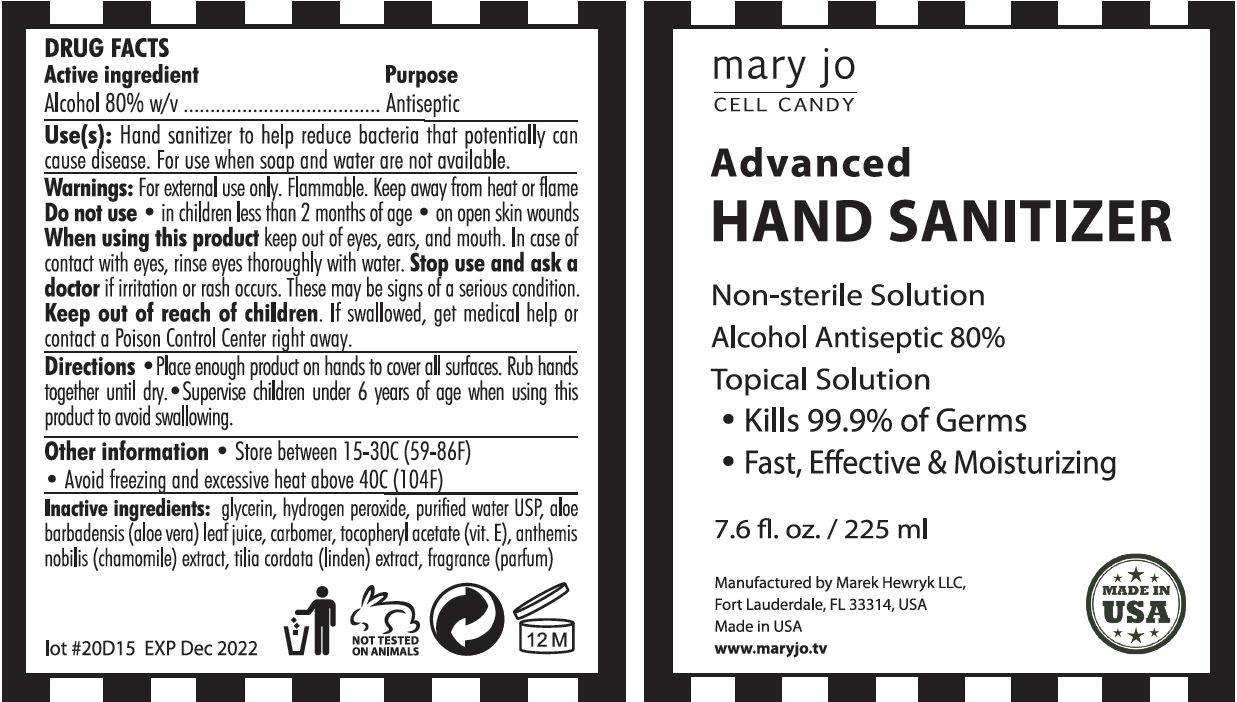 DRUG LABEL: MARY JO - CELL CANDY - ADVANCED HAND SANITIZER
NDC: 75161-102 | Form: GEL
Manufacturer: MAREK HEWRYK LLC
Category: otc | Type: HUMAN OTC DRUG LABEL
Date: 20200529

ACTIVE INGREDIENTS: ALCOHOL 80 mL/100 mL
INACTIVE INGREDIENTS: GLYCERIN; HYDROGEN PEROXIDE; WATER; ALOE VERA LEAF; CARBOMER HOMOPOLYMER, UNSPECIFIED TYPE; .ALPHA.-TOCOPHEROL ACETATE; CHAMAEMELUM NOBILE FLOWER; TILIA CORDATA FLOWER

MARY JO - CELL CANDY - ADVANCED HAND SANITIZER - ALCOHOL 80%

ACTIVE INGREDIENT

ALCOHOL 80% W/V

PURPOSE

ANTISEPTIC

USE(S)

HAND SANITIZER TO HELP REDUCE BACTERIA THAT POTENTIALLY CAN CAUSE DISEASE. FOR USE WHEN SOAP AND WATER ARE NOT AVAILABLE.

WARNINGS

FOR EXTERNAL USE ONLY. FLAMMABLE. KEEP AWAY FROM HEAT OR FLAME.

DO NOT USE

- IN CHILDREN LESS THAN 2 MONTHS OF AGE
- ON OPEN SKIN WOUNDS

WHEN USING THIS PRODUCT KEEP OUT OF EYES, EARS, AND MOUTH. IN CASE OF CONTACT WITH EYES, RINSE EYES THOROUGHLY WITH WATER.

STOP USE AND ASK A DOCTOR IF IRRITATION OR RASH OCCURS. THESE MAY BE SIGNS OF A SERIOUS CONDITION.

KEEP OUT OF REACH OF CHILDREN.

IF SWALLOWED, GET MEDICAL HELP OR CONTACT A POISON CONTROL CENTER RIGHT AWAY.

DIRECTIONS

- PLACE ENOUGH PRODUCT ON HANDS TO COVER ALL SURFACES. RUB HANDS TOGETHER UNTIL DRY.
- SUPERVISE CHILDREN UNDER 6 YEARS OF AGE WHEN USING THIS PRODUCT TO AVOID SWALLOWING.

OTHER INFORMATION

- STORE BETWEEN 15-30C (59-86F)
- AVOID FREEZING AND EXCESSIVE HEAT ABOVE 40C (104F)

INACTIVE INGREDIENTS

GLYCERIN, HYDROGEN PEROXIDE, PURIFIED WATER USP, ALOE BARBADENSIS (ALOE VERA) LEAF JUICE, CARBOMER, TOCOPHERYL ACETATE (VIT. E), ANTHEMIS NOBILIS (CHAMOMILE) EXTRACT, TILIA CORDATA (LINDEN) EXTRACT, FRAGRANCE (PARFUM)